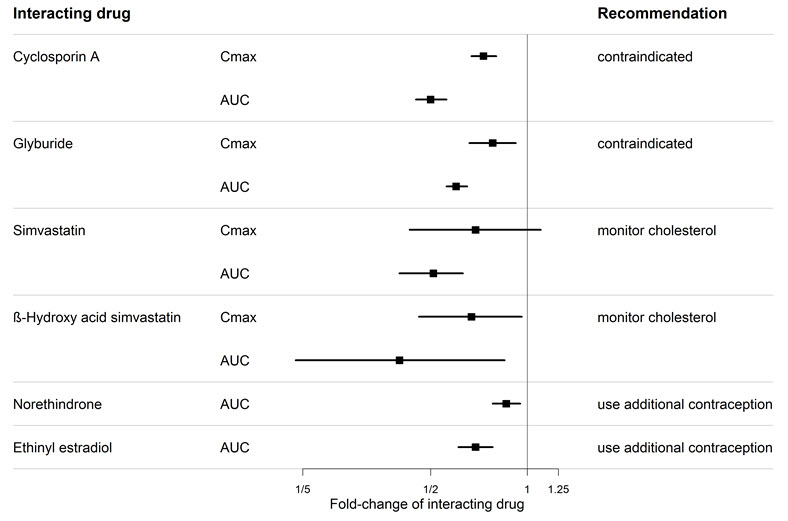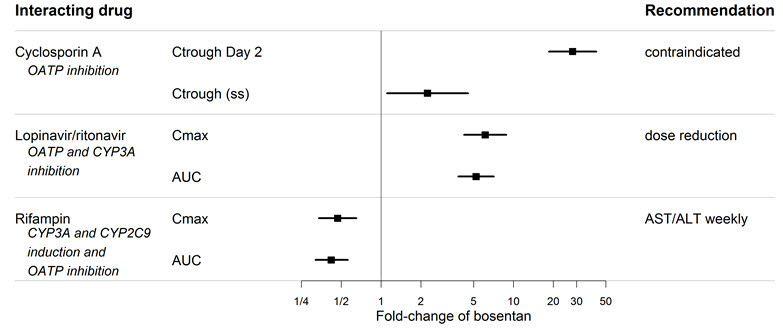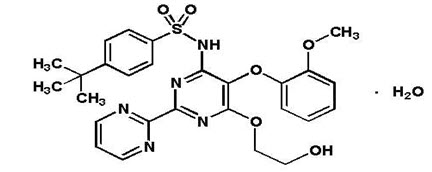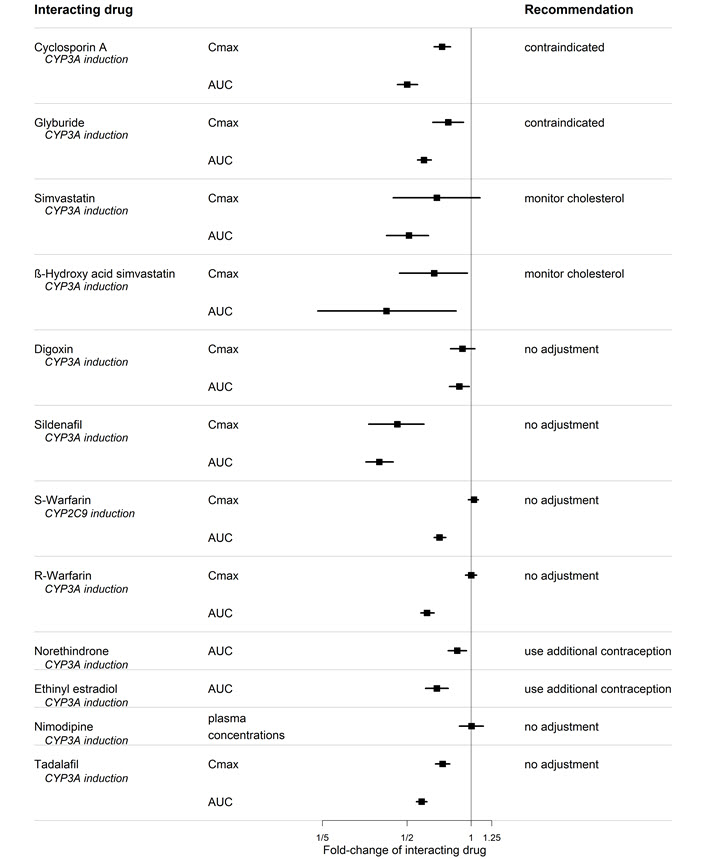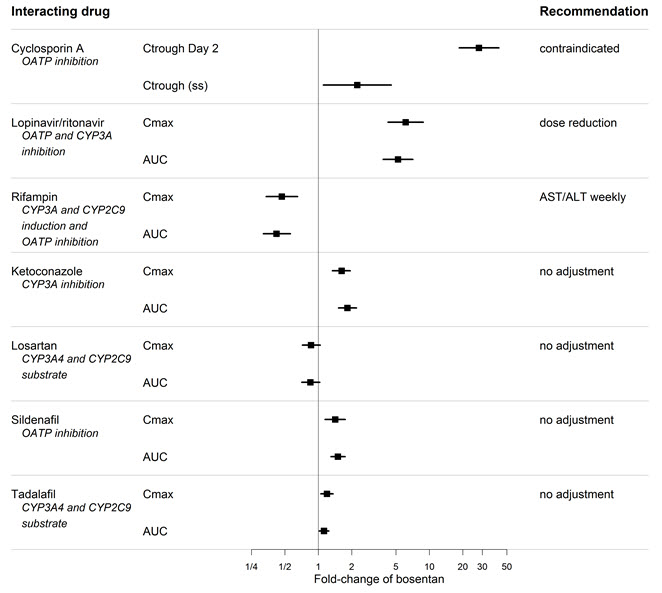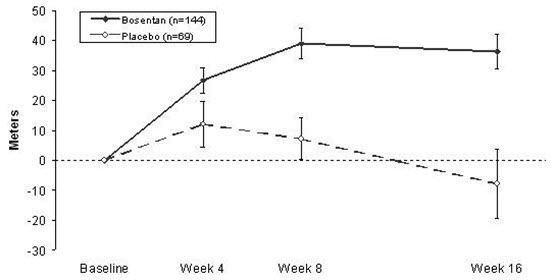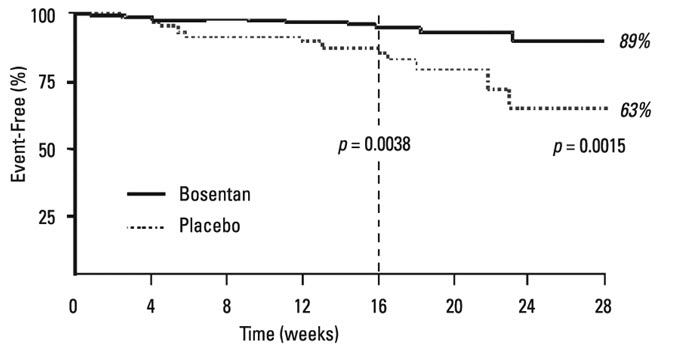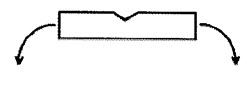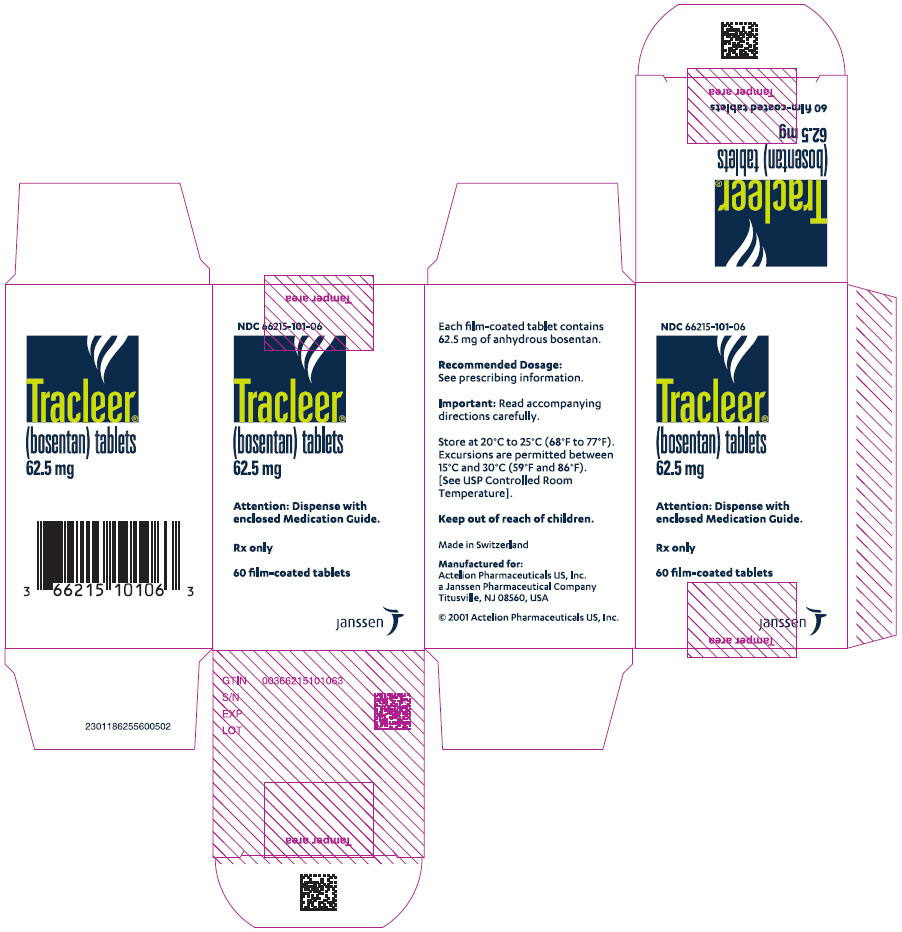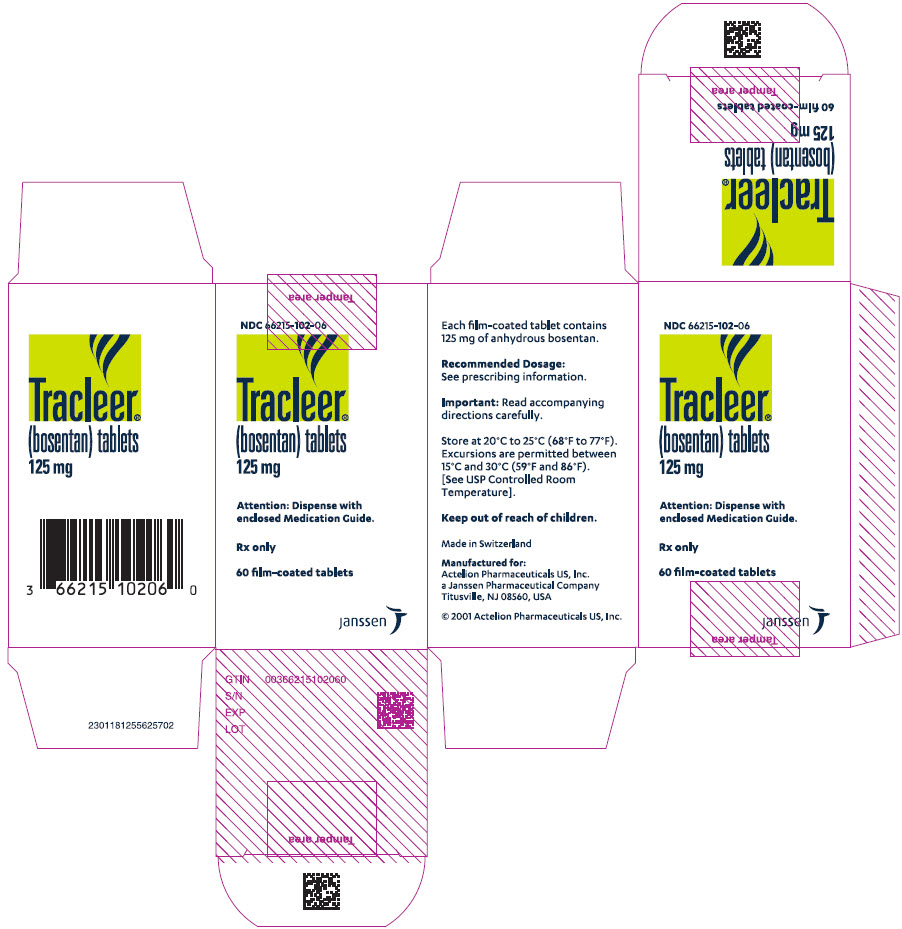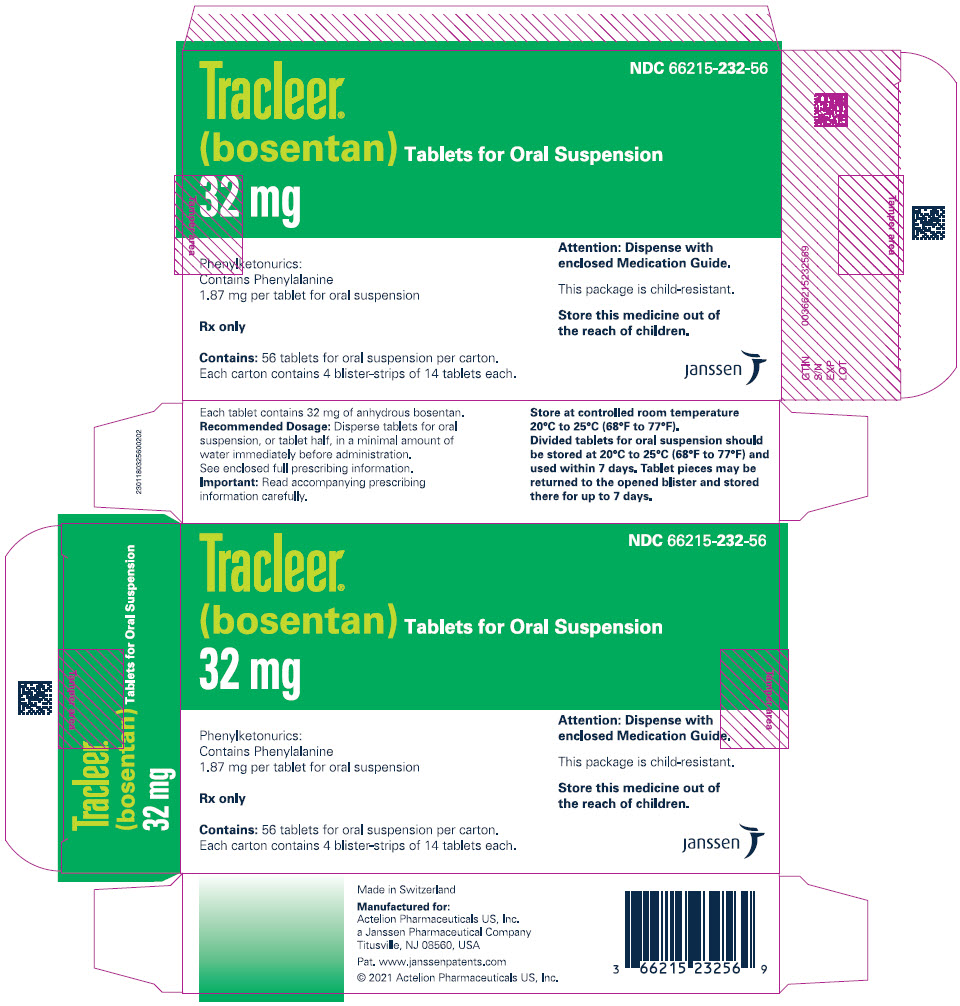 DRUG LABEL: Tracleer
NDC: 66215-101 | Form: TABLET, FILM COATED
Manufacturer: Actelion Pharmaceuticals US, Inc.
Category: prescription | Type: HUMAN PRESCRIPTION DRUG LABEL
Date: 20251117

ACTIVE INGREDIENTS: BOSENTAN 62.5 mg/1 1
INACTIVE INGREDIENTS: SODIUM STARCH GLYCOLATE TYPE A POTATO; POVIDONE K90; GLYCERYL DIBEHENATE; MAGNESIUM STEARATE; HYPROMELLOSE, UNSPECIFIED; TRIACETIN; TALC; TITANIUM DIOXIDE; FERRIC OXIDE YELLOW; FERRIC OXIDE RED; ETHYLCELLULOSE, UNSPECIFIED; STARCH, CORN

HIGHLIGHTS OF PRESCRIBING INFORMATION

These highlights do not include all the information needed to use TRACLEER safely and effectively. See full prescribing information for TRACLEER.
TRACLEER®(bosentan) tablets, for oral use
TRACLEER®(bosentan) tablets for oral suspension
Initial U.S. Approval: 2001

WARNING: RISKS OF HEPATOTOXICITY and EMBRYO-FETAL TOXICITY

See full prescribing information for complete boxed warning.

TRACLEER is available only through a restricted distribution program called the Bosentan Risk Evaluation and Mitigation Strategy (REMS) because of the risk of hepatotoxicity (5.2):

Elevations of liver aminotransferases (ALT, AST) and liver failure have been reported with TRACLEER (5.1).

- Measure liver aminotransferases prior to initiation of treatment and then monthly (2.1, 5.1).
- Discontinue TRACLEER if aminotransferase elevations are accompanied by signs or symptoms of liver dysfunction or injury or increases in bilirubin ≥2×ULN (2.4, 5.1).

Based on animal data, TRACLEER may cause fetal harm if used during pregnancy (4.1, 5.3, 8.1).

- Females of reproductive potential: Exclude pregnancy before initiating treatment. Use effective contraception prior to initiation of treatment, during treatment and for one month after stopping TRACLEER (2.1, 4.1, 5.3, 8.1, 8.3).
- When pregnancy is detected, discontinue TRACLEER as soon as possible (5.3).

RECENT MAJOR CHANGES

Boxed Warning | 11/2025
Dosage and Administration (2.1) | 11/2025
Contraindications (4.1) | 11/2025
Warnings and Precautions (5.1, 5.2, 5.3) | 11/2025

1 INDICATIONS AND USAGE

TRACLEER is an endothelin receptor antagonist indicated for the treatment of pulmonary arterial hypertension (PAH) (WHO Group 1):

- in adults to improve exercise ability and to decrease clinical worsening. Studies establishing effectiveness included predominantly patients with WHO Functional Class II-IV symptoms and etiologies of idiopathic or heritable PAH (60%), PAH associated with connective tissue diseases (21%), and PAH associated with congenital heart disease with left-to-right shunts (18%) (1).
- in pediatric patients aged 3 years and older with idiopathic or congenital PAH to improve pulmonary vascular resistance (PVR), which is expected to result in an improvement in exercise ability (1).

2 DOSAGE AND ADMINISTRATION

- Patients older than 12 years of age: initiate at 62.5 mg orally twice daily; for patients weighing greater than 40 kg, increase to 125 mg orally twice daily after 4 weeks (2.2).
- Patients 12 years of age and younger: dosage is based on weight, see Table 1(2.2).
- Reduce the dose and closely monitor patients developing aminotransferase elevations more than 3×Upper Limit of Normal (ULN) (2.4).

3 DOSAGE FORMS AND STRENGTHS

- Film-coated tablet: 62.5 mg and 125 mg (3).
- Tablet for oral suspension: 32 mg (3).

4 CONTRAINDICATIONS

- Pregnancy (4.1).
- Use with Cyclosporine A (4.2).
- Use with Glyburide (4.3).
- Hypersensitivity (4.4).

5 WARNINGS AND PRECAUTIONS

- Fluid retention: May require intervention (5.4).
- Pulmonary veno-occlusive disease (PVOD): If signs of pulmonary edema occur, consider the diagnosis of associated PVOD and consider discontinuing TRACLEER (5.5).
- Decreased sperm counts (5.6).
- Decreases in hemoglobin and hematocrit: Monitor hemoglobin levels after 1 and 3 months of treatment, then every 3 months thereafter (5.7).

6 ADVERSE REACTIONS

- Common adverse reactions (≥3% more than placebo) for the film-coated tablet are respiratory tract infection and anemia (6.1).
- Common adverse reactions (≥15%) for the dispersible tablet are upper respiratory tract infections and pyrexia (6.1).

To report SUSPECTED ADVERSE REACTIONS, contact Actelion at 1-800-526-7736 or FDA at 1-800-FDA-1088 or www.fda.gov/medwatch.

7 DRUG INTERACTIONS

- Cytochrome P450: Coadministration of TRACLEER with drugs metabolized by CYP2C9 and CYP3A can increase exposure to TRACLEER and/or the coadministered drug (4.2, 4.3, 7.1).
- Hormonal contraceptives: TRACLEER use decreases contraceptive exposure and reduces effectiveness (7.2).

8 USE IN SPECIFIC POPULATIONS

- Nursing mothers: Choose breastfeeding or TRACLEER (8.2).

FULL PRESCRIBING INFORMATION

WARNING: RISKS OF HEPATOTOXICITY and EMBRYO-FETAL TOXICITY

Because of the risk of hepatotoxicity, TRACLEER is available only through a restricted program called the Bosentan Risk Evaluation and Mitigation Strategy (REMS). Under the Bosentan REMS, prescribers, patients, and pharmacies must enroll in the program [see Warnings and Precautions (5.2)] .

Hepatotoxicity

In clinical studies, TRACLEER caused at least 3-fold upper limit of normal (ULN) elevation of liver aminotransferases (ALT and AST) in about 11% of patients, accompanied by elevated bilirubin in a small number of cases. Because these changes are a marker for potential serious hepatotoxicity, serum aminotransferase levels must be measured prior to initiation of treatment and then monthly [see Dosage and Administration (2.4), Warnings and Precautions (5.1)] . In the postmarketing period, in the setting of close monitoring, rare cases of unexplained hepatic cirrhosis were reported after prolonged (>12 months) therapy with TRACLEER in patients with multiple comorbidities and drug therapies. There have also been reports of liver failure. The contribution of TRACLEER in these cases could not be excluded.

In at least one case, the initial presentation (after >20 months of treatment) included pronounced elevations in aminotransferases and bilirubin levels accompanied by non-specific symptoms, all of which resolved slowly over time after discontinuation of TRACLEER. This case reinforces the importance of strict adherence to the monthly monitoring schedule for the duration of treatment and the treatment algorithm, which includes stopping TRACLEER with a rise of aminotransferases accompanied by signs or symptoms of liver dysfunction [see Dosage and Administration (2.4)] .

Elevations in aminotransferases require close attention [see Dosage and Administration (2.4)] . TRACLEER should generally be avoided in patients with elevated aminotransferases (>3×ULN) at baseline because monitoring for hepatotoxicity may be more difficult. If liver aminotransferase elevations are accompanied by clinical symptoms of hepatotoxicity (such as nausea, vomiting, fever, abdominal pain, jaundice, or unusual lethargy or fatigue) or increases in bilirubin ≥2×ULN, treatment with TRACLEER should be stopped. There is no experience with the reintroduction of TRACLEER in these circumstances.

Embryo-Fetal Toxicity

TRACLEER is contraindicated for use during pregnancy because it may cause fetal harm if used by pregnant females based on animal data. Therefore, for females of reproductive potential, exclude pregnancy before the start of treatment with TRACLEER. Advise use of effective contraception before initiation, during treatment and for one month after stopping TRACLEER. When pregnancy is detected, discontinue TRACLEER as soon as possible [see Dosage and Administration (2.1), Contraindications (4.1), Warnings and Precautions (5.3), Drug Interactions (7.2), Use in Specific Populations (8.1, 8.3)].

1 INDICATIONS AND USAGE

TRACLEER is indicated for the treatment of pulmonary arterial hypertension (PAH) (WHO Group 1):

- in adults to improve exercise ability and to decrease clinical worsening. Studies establishing effectiveness included predominantly patients with WHO Functional Class II-IV symptoms and etiologies of idiopathic or heritable PAH (60%), PAH associated with connective tissue diseases (21%), and PAH associated with congenital heart disease with left-to-right shunts (18%) [see Clinical Studies (14.1)] .
- in pediatric patients aged 3 years and older with idiopathic or congenital PAH to improve pulmonary vascular resistance (PVR), which is expected to result in an improvement in exercise ability.

2 DOSAGE AND ADMINISTRATION

2.1 Required Monitoring

Healthcare professionals who prescribe TRACLEER must enroll in the Bosentan REMS and must comply with the required monitoring to minimize the risks associated with TRACLEER [see Warnings and Precautions (5.2)].

Measure liver aminotransferase levels prior to initiation of treatment and then monthly [see Boxed Warning, Warnings and Precautions (5.1, 5.2)].

Exclude pregnancy before initiating treatment with TRACLEER in females of reproductive potential [see Boxed Warning, Contraindications (4.1), Warnings and Precautions (5.3), Use in Specific Populations (8.1, 8.3)] .

2.2 Recommended Dosage

Administer TRACLEER orally following the dosing recommendations in Table 1. Doses above 125 mg twice daily did not appear to confer additional benefit sufficient to offset the increased risk of hepatotoxicity.

Table 1: Dosing Recommendations
 | Initial 4 weeks | Maintenance (after 4 weeks)
Patients >12 years of age and >40 kg | 62.5 mg twice daily | 125 mg twice daily
Patients >12 years of age and <40 kg | 62.5 mg twice daily | 62.5 mg twice daily
Patients ≤12 years of age
≥4–8 kg | 16 mg twice daily | 16 mg twice daily
>8–16 kg | 32 mg twice daily | 32 mg twice daily
>16–24 kg | 48 mg twice daily | 48 mg twice daily
>24–40 kg | 64 mg twice daily | 64 mg twice daily

2.3 Administration

TRACLEER film-coated tablets and tablets for oral suspension (dispersible tablets) should be administered orally twice daily.

Disperse tablets for oral suspension, or dispersible tablet half, in a minimal amount of water immediately before administration.

Store divided dispersible tablet pieces at 20 ºC to 25 ºC (68 ºF to 77 ºF) in the opened blister for up to 7 days.

2.4 Dosage Adjustments for Aminotransferase Elevations

If aminotransferase levels increase, adjust monitoring and treatment plan according to Table 2.

Discontinue TRACLEER if liver aminotransferase elevations are accompanied by clinical symptoms of hepatotoxicity (such as nausea, vomiting, fever, abdominal pain, jaundice, or unusual lethargy or fatigue) or bilirubin ≥2 ×Upper Limit of Normal (ULN). There is no experience with the reintroduction of TRACLEER in these circumstances.

Table 2: Dosage Adjustment and Monitoring in Patients Developing Aminotransferase Elevations >3×ULN
ALT/AST levels | Treatment and monitoring recommendations
>3 and ≤5 ×ULN | Confirm by another aminotransferase test; if confirmed,; - in adults and pediatric patients >12 years and >40 kg, reduce the daily dose to 62.5 mg twice daily or interrupt treatment, and monitor aminotransferase levels at least every 2 weeks. If the aminotransferase levels return to pretreatment values, treatment may continue or be reintroduced at 62.5 mg twice daily, with reassessment of aminotransferase levels within 3 days. - in all other pediatric patients, interrupt treatment with no prior dose reduction. If the aminotransferase levels return to pretreatment values, reintroduce at the dose used prior to treatment interruption, with reassessment of aminotransferase levels within 3 days.
>5 and ≤8 ×ULN | Confirm by another aminotransferase test; if confirmed, stop treatment and monitor aminotransferase levels at least every 2 weeks. Once the aminotransferase levels return to pretreatment values,; - in adults and pediatric patients >12 years and >40 kg, consider reintroduction of treatment at 62.5 mg twice daily, with reassessment of aminotransferase levels within 3 days. - in all other pediatric patients, consider reintroduction at the dose used prior to treatment interruption, with reassessment of aminotransferase levels within 3 days.
>8 ×ULN | Stop treatment permanently. There is no experience with reintroduction of TRACLEER in these circumstances.

2.5 Use with Ritonavir

Co-administration of TRACLEER in Patients on Ritonavir

In patients who have been receiving ritonavir for at least 10 days, start TRACLEER at the recommended initial dose once daily or every other day based upon individual tolerability [see Drug Interactions (7.1)] .

Co-administration of Ritonavir in Patients on TRACLEER

Discontinue use of TRACLEER at least 36 hours prior to initiation of ritonavir. After at least 10 days following the initiation of ritonavir, resume TRACLEER at the recommended initial dose once daily or every other day based upon individual tolerability [see Drug Interactions (7.1)] .

2.6 Use in Patients with Pre-existing Hepatic Impairment

Avoid initiation of TRACLEER in patients with aminotransferases >3 ×ULN. No dose adjustment is required in patients with mildly impaired liver function [see Warnings and Precautions (5.1), Use in Specific Populations (8.6), Clinical Pharmacology (12.3)] .

3 DOSAGE FORMS AND STRENGTHS

62.5 mg tablets: round, biconvex, orange-white tablets, debossed with identification marking "62,5"

125 mg tablets: oval, biconvex, orange-white tablets, debossed with identification marking "125"

32 mg tablets for oral suspension: round, pale yellow to off-white tablets, bisected on one side and debossed with identification marking “32” on the other side.

4 CONTRAINDICATIONS

4.1 Pregnancy

Use of TRACLEER is contraindicated in females who are pregnant [see Boxed Warning, Dosage and Administration (2.1), Warnings and Precautions (5.3), Use in Specific Populations (8.1)].

4.2 Use with Cyclosporine A

Co-administration of cyclosporine A and bosentan resulted in markedly increased plasma concentrations of bosentan. Therefore, concomitant use of TRACLEER and cyclosporine A is contraindicated [see Drug Interactions (7.1)] .

4.3 Use with Glyburide

An increased risk of liver enzyme elevations was observed in patients receiving glyburide concomitantly with bosentan. Therefore co-administration of glyburide and TRACLEER is contraindicated [see Drug Interactions (7.1)] .

4.4 Hypersensitivity

TRACLEER is contraindicated in patients who are hypersensitive to bosentan or any component of the product. Observed reactions include Drug Reaction with Eosinophilia and Systemic Symptoms (DRESS), anaphylaxis, rash, and angioedema [see Adverse Reactions (6.2), Description (11)] .

5 WARNINGS AND PRECAUTIONS

5.1 Hepatotoxicity

ALT or AST >3 ×ULN were observed in 11% of TRACLEER-treated patients (n=658) compared to 2% of placebo-treated patients (n=280). Three-fold increases were seen in 12% of 95 pulmonary arterial hypertension (PAH) patients on 125 mg twice daily and 14% of 70 PAH patients on 250 mg twice daily. Eight-fold increases were seen in 2% of PAH patients on 125 mg twice daily and 7% of PAH patients on 250 mg twice daily. Bilirubin increases to ≥3 ×ULN were associated with aminotransferase increases in 2 of 658 (0.3%) of patients treated with TRACLEER. In a pooled analysis of four pediatric studies conducted in PAH (n=100), elevations in liver aminotransferases ≥3×ULN were observed in 2% of patients. The combination of hepatocellular injury (increases in aminotransferases of >3 ×ULN) and increases in total bilirubin (≥2 ×ULN) is a marker for potential serious hepatotoxicity.

Elevations of AST or ALT associated with TRACLEER are dose-dependent, occur both early and late in treatment, usually progress slowly, are typically asymptomatic, and usually have been reversible after treatment interruption or cessation. Aminotransferase elevations also may reverse spontaneously while continuing treatment with TRACLEER.

Liver aminotransferase levels must be measured prior to initiation of treatment and then monthly and therapy adjusted accordingly [see Dosage and Administration (2.1, 2.4)] . Discontinue TRACLEER if liver aminotransferase elevations are accompanied by clinical symptoms of hepatotoxicity (such as nausea, vomiting, fever, abdominal pain, jaundice, or unusual lethargy or fatigue) or increases in bilirubin ≥2 ×ULN.

Avoid initiation of TRACLEER in patients with elevated aminotransferases (>3 ×ULN) prior to drug initiation because monitoring hepatotoxicity in these patients may be more difficult [see Boxed Warning, Dosage and Administration (2.6), Use in Specific Populations (8.6)] .

In WHO Functional Class II patients, consider whether the benefits of TRACLEER are sufficient to offset the risk of hepatotoxicity, which may preclude future use as their disease progresses.

TRACLEER is only available through a restricted program under REMS [see Warnings and Precautions (5.2)].

5.2 Bosentan REMS

Because of the risks of hepatotoxicity , TRACLEER is available only through a restricted program called the Bosentan REMS. As a component of the Bosentan REMS, prescribers, patients, and pharmacies must enroll in the program [see Boxed Warning, Warnings and Precautions (5.1)] .

Required components of the Bosentan REMS are:

- Healthcare professionals who prescribe TRACLEER must review the prescriber educational materials, enroll in the Bosentan REMS and comply with its requirements.
- Healthcare professionals must (1) review serum aminotransferases (ALT/AST) and bilirubin, and agree to order and monitor these tests monthly.
- To receive TRACLEER, all patients must understand the risks and benefits, and complete a patient enrollment form with their prescriber.
- Pharmacies that dispense TRACLEER must enroll in the program and agree to comply with the Bosentan REMS requirements.

Further information about TRACLEER and the Bosentan REMS is available at www.BosentanREMSProgram.com or 1-866-359-2612.

5.3 Embryo-Fetal Toxicity

Based on data from animal reproduction studies, TRACLEER may cause fetal harm when administered to a pregnant female and is contraindicated in females who are pregnant. The available human data for endothelin receptor antagonists do not establish the presence or absence of major birth defects related to the use of TRACLEER. Advise females of reproductive potential about the potential risk to a fetus. Exclude pregnancy prior to TRACLEER treatment. Advise females of reproductive potential to use effective contraception prior to initiation of treatment with TRACLEER, during treatment, and for at least one month after the last dose. When pregnancy is detected, discontinue TRACLEER as soon as possible [see Dosage and Administration (2.1), Contraindications (4.1), Drug Interactions (7.2), Use in Specific Populations (8.1, 8.3)].

5.4 Fluid Retention

Peripheral edema is a known clinical consequence of PAH and worsening PAH and is also a known effect of TRACLEER and other endothelin receptor antagonists. In PAH clinical trials with TRACLEER, combined adverse events of fluid retention or edema were reported in 1.7% (placebo-corrected) of patients.

In addition, there have been numerous postmarketing reports of fluid retention in patients with pulmonary hypertension occurring within weeks after starting TRACLEER. Patients required intervention with a diuretic, fluid management, or hospitalization for decompensating heart failure.

If clinically significant fluid retention develops, with or without associated weight gain, further evaluation should be undertaken to determine the cause, such as TRACLEER or underlying heart failure, and the possible need for treatment or discontinuation of TRACLEER [see Adverse Reactions (6.1), Clinical Studies (14.2)] .

5.5 Pulmonary Veno-Occlusive Disease

If signs of pulmonary edema occur, consider the possibility of associated pulmonary veno-occlusive disease and consider whether TRACLEER should be discontinued.

5.6 Decreased Sperm Counts

Decreased sperm counts have been observed in patients receiving TRACLEER. Preclinical data also suggest that TRACLEER, similar to other endothelin receptor antagonists, may have an adverse effect on spermatogenesis [see Adverse Reactions (6.1), Nonclinical Toxicology (13.1)] .

5.7 Decreases in Hemoglobin and Hematocrit

Treatment with TRACLEER can cause a dose-related decrease in hemoglobin and hematocrit. There have been postmarketing reports of decreases in hemoglobin concentration and hematocrit that have resulted in anemia requiring transfusion. It is recommended that hemoglobin concentrations be checked after 1 and 3 months, and every 3 months thereafter. If a marked decrease in hemoglobin concentration occurs, further evaluation should be undertaken to determine the cause and need for specific treatment [see Adverse Reactions (6.1)] .

6 ADVERSE REACTIONS

The following important adverse reactions are described elsewhere in the labeling:

- Hepatotoxicity [see Boxed Warning, Warnings and Precautions (5.1)]
- Embryo-fetal Toxicity [see Boxed Warning, Warnings and Precautions (5.3)]
- Fluid Retention [see Warnings and Precautions (5.4)]

6.1 Clinical Trials Experience

Because clinical trials are conducted under widely varying conditions, adverse reaction rates observed in the clinical trials of a drug cannot be directly compared to rates in the clinical trials of another drug and may not reflect the rates observed in practice.

Safety data on TRACLEER were obtained from 13 clinical studies (9 placebo-controlled and 4 open-label) in 870 adult patients with PAH and other diseases. Doses up to 8 times the currently recommended clinical dose (125 mg twice daily) were administered for a variety of durations. The exposure to TRACLEER in these trials ranged from 1 day to 4.1 years (n=94 for 1 year; n=61 for 1.5 years; and n=39 for more than 2 years). Exposure of PAH patients (n=328) to TRACLEER ranged from 1 day to 1.7 years (n=174 more than 6 months and n=28 more than 12 months).

Treatment discontinuations due to adverse events other than those related to pulmonary hypertension during the clinical trials in adult patients with PAH were more frequent on TRACLEER (6%; 15/258 patients) than on placebo (3%; 5/172 patients). In this database the only cause of discontinuations >1% and occurring more often on TRACLEER was abnormal liver function.

The adverse drug events that occurred in ≥3% of the TRACLEER-treated patients and were more common on TRACLEER in placebo-controlled trials in PAH at doses of 125 or 250 mg twice daily are shown in Table 3:

Table 3: Adverse Events [Note: only AEs with onset from start of treatment to 1 calendar day after end of treatment are included. All reported events (at least 3%) are included except those too general to be informative, and those not reasonably associated with the use of the drug because they were associated with the condition being treated or are very common in the treated population.] Occurring in ≥3% of Patients Treated with TRACLEER 125-250 mg Twice Daily and More Common on TRACLEER in Placebo-Controlled Studies in Pulmonary Arterial Hypertension
Adverse Event | TRACLEER n=258 |  | Placebo n=172
 | No. | % | No. | %
Respiratory Tract Infection [Respiratory Tract Infection combines the terms "Nasopharyngitis", "Upper Respiratory Tract Infection" and "Respiratory Tract Infection". Combined data from Study 351, BREATHE-1 and EARLY] | 56 | 22% | 30 | 17%
Headache | 39 | 15% | 25 | 14%
Edema | 28 | 11% | 16 | 9%
Chest Pain | 13 | 5% | 8 | 5%
Syncope | 12 | 5% | 7 | 4%
Flushing | 10 | 4% | 5 | 3%
Hypotension | 10 | 4% | 3 | 2%
Sinusitis | 9 | 4% | 4 | 2%
Arthralgia | 9 | 4% | 3 | 2%
Serum Aminotransferases, abnormal | 9 | 4% | 3 | 2%
Palpitations | 9 | 4% | 3 | 2%
Anemia | 8 | 3% | - | -

TRACLEER was evaluated for safety in 119 pediatric patients in uncontrolled studies. The safety profile was similar to that observed in adult patients with PAH.

Decreased Sperm Counts

An open-label, single-arm, multicenter, safety study evaluated the effect on testicular function of TRACLEER 62.5 mg twice daily for 4 weeks, followed by 125 mg twice daily for 5 months. Twenty-five male patients with WHO functional class III and IV PAH and normal baseline sperm count were enrolled. Twenty-three completed the study and 2 discontinued due to adverse events not related to testicular function. There was a decline in sperm count of at least 50% in 25% of the patients after 3 or 6 months of treatment with TRACLEER. Sperm count remained within the normal range in all 22 patients with data after 6 months and no changes in sperm morphology, sperm motility, or hormone levels were observed. One patient developed marked oligospermia at 3 months and the sperm count remained low with 2 follow-up measurements over the subsequent 6 weeks. TRACLEER was discontinued and after 2 months the sperm count had returned to baseline levels. Based on these findings and preclinical data from endothelin receptor antagonists, it cannot be excluded that endothelin receptor antagonists such as TRACLEER have an adverse effect on spermatogenesis.

Decreases in Hemoglobin and Hematocrit

Treatment with TRACLEER can cause a dose-related decrease in hemoglobin and hematocrit. It is recommended that hemoglobin concentrations be checked after 1 and 3 months, and every 3 months thereafter. If a marked decrease in hemoglobin concentration occurs, further evaluation should be undertaken to determine the cause and need for specific treatment.

The overall mean decrease in hemoglobin concentration for adult TRACLEER-treated patients was 0.9 g/dL (change to end of treatment). Most of this decrease of hemoglobin concentration was detected during the first few weeks of TRACLEER treatment and hemoglobin levels stabilized by 4–12 weeks of TRACLEER treatment. In placebo-controlled studies of all uses of TRACLEER, marked decreases in hemoglobin (>15% decrease from baseline resulting in values <11 g/dL) were observed in 6% of TRACLEER-treated patients and 3% of placebo-treated patients. In patients with PAH treated with doses of 125 and 250 mg twice daily, marked decreases in hemoglobin occurred in 3% compared to 1% in placebo-treated patients.

A decrease in hemoglobin concentration by at least 1 g/dL was observed in 57% of TRACLEER-treated patients as compared to 29% of placebo-treated patients. In 80% of those patients whose hemoglobin decreased by at least 1 g/dL, the decrease occurred during the first 6 weeks of TRACLEER treatment.

During the course of treatment, the hemoglobin concentration remained within normal limits in 68% of TRACLEER-treated patients compared to 76% of placebo patients. The explanation for the change in hemoglobin is not known, but it does not appear to be hemorrhage or hemolysis.

In a pooled analysis of pediatric patients (N=100) with PAH treated with TRACLEER, a decrease in hemoglobin levels to <10 g/dL from baseline was reported in 11% of patients. There was no decrease to <8 g/dL.

6.2 Postmarketing Experience

There have been several postmarketing reports of angioedema associated with the use of TRACLEER. The onset of the reported cases occurred within a range of 8 hours to 21 days after starting therapy. Some patients were treated with an antihistamine and their signs of angioedema resolved without discontinuing TRACLEER.

The following additional adverse reactions have been reported during the post approval use of TRACLEER. Because these adverse reactions are reported from a population of uncertain size, it is not always possible to reliably estimate their frequency or establish a causal relationship to TRACLEER exposure:

- Unexplained hepatic cirrhosis [see Boxed Warning]
- Liver failure [see Boxed Warning]
- Hypersensitivity, DRESS, and anaphylaxis [see Contraindications (4.4)]
- Thrombocytopenia
- Rash
- Jaundice
- Anemia requiring transfusion
- Neutropenia and leukopenia
- Nasal congestion
- Autoimmune hepatitis

7 DRUG INTERACTIONS

7.1 Cytochrome P450 Drug Interactions

Bosentan is metabolized by CYP2C9 and CYP3A. Inhibition of these enzymes may increase the plasma concentration of bosentan [see Clinical Pharmacology (12.3)] . Concomitant administration of both a CYP2C9 inhibitor (such as fluconazole or amiodarone) and a strong CYP3A inhibitor (e.g., ketoconazole, itraconazole) or a moderate CYP3A inhibitor (e.g., amprenavir, erythromycin, fluconazole, diltiazem) with TRACLEER will likely lead to large increases in plasma concentrations of bosentan. Co-administration of such combinations of a CYP2C9 inhibitor plus a strong or moderate CYP3A inhibitor with TRACLEER is not recommended.

Bosentan is an inducer of CYP3A and CYP2C9. Consequently plasma concentrations of drugs metabolized by these two isozymes will be decreased when TRACLEER is co-administered. Bosentan had no relevant inhibitory effect on any CYP isozyme in vitro(CYP1A2, CYP2C9, CYP2C19, CYP2D6, CYP3A). Consequently, TRACLEER is not expected to increase the plasma concentrations of drugs metabolized by these enzymes.

Figure 1. CYP3A induction-mediated effect of bosentan on other drugs

Figure 2. Effect of other drugs on bosentan

7.2 Hormonal Contraceptives

Hormonal contraceptives, including oral, injectable, transdermal, and implantable forms, may not be reliable when TRACLEER is co-administered. Females should practice additional methods of contraception and not rely on hormonal contraception alone when taking TRACLEER [see Use in Specific Populations (8.3)] .

An interaction study demonstrated that co-administration of bosentan and a combination oral hormonal contraceptive produced average decreases of norethindrone and ethinyl estradiol levels of 14% and 31%, respectively. However, decreases in exposure were as much as 56% and 66%, respectively, in individual subjects.

8 USE IN SPECIFIC POPULATIONS

8.1 Pregnancy

Risk Summary

Based on data from animal reproduction studies, TRACLEER may cause fetal harm, including birth defects and fetal death, when administered to a pregnant female and is contraindicated during pregnancy [see Contraindications (4.1)] . Available data from postmarketing reports and published literature over decades of use with endothelin receptor antagonists (ERA) in the same class as TRACLEER have not identified an increased risk of major birth defects; however, these data are limited. Methodological limitations of these postmarketing reports and published literature include lack of a control group; limited information regarding dose, duration, and timing of drug exposure; and missing data. These limitations preclude establishing a reliable estimate of the risk of adverse fetal and neonatal outcomes with maternal ERA use. In animal reproduction studies, oral administration of bosentan to pregnant rats at 2-times the maximum recommended human dose (MRHD) on a mg/m^2 basis caused teratogenic effects in rats, including malformations of the head, mouth, face, and large blood vessels [see Animal Data] . Advise pregnant women of the potential risk to a fetus.

The estimated background risk of major birth defects and miscarriage for the indicated population is unknown. All pregnancies have a background risk of birth defect, loss, or other adverse outcomes. In the U.S. general population, the estimated background risk of major birth defects and miscarriage in clinically recognized pregnancies is 2–4% and 15–20%, respectively.

Data

Animal Data

Bosentan was teratogenic in rats given oral doses two times the MRHD (on a mg/m^2 basis). In an embryo-fetal toxicity study in rats, bosentan showed dose-dependent teratogenic effects, including malformations of the head, mouth, face and large blood vessels. Bosentan increased stillbirths and pup mortality at oral doses 2 and 10 times the MRHD (on a mg/m^2 basis). Although birth defects were not observed in rabbits given oral doses of up to the equivalent of 10.5 g/day in a 70 kg person, plasma concentrations of bosentan in rabbits were lower than those reached in the rat. The similarity of malformations induced by bosentan and those observed in endothelin-1 knockout mice and in animals treated with other endothelin receptor antagonists indicates that embryo-fetal toxicity is a class effect of these drugs.

8.2 Lactation

Risk Summary

Data from a case report describe the presence of bosentan in human milk. There is insufficient information about the effects of bosentan on the breastfed infant and no information on the effects of bosentan on milk production. Because of the potential for serious adverse reactions, such as fluid retention and hepatotoxicity, in breastfed infants from TRACLEER, advise women not to breastfeed during treatment with TRACLEER.

8.3 Females and Males of Reproductive Potential

Based on data from animal reproductive toxicity studies, TRACLEER may cause fetal harm, including birth defects and fetal death, when administered to a pregnant patient and is contraindicated during pregnancy [see Contraindications (4.1), Use in Specific Populations (8.1)].

Pregnancy Testing

Verify that females of reproductive potential are not pregnant prior to initiating TRACLEER. The patient should contact her physician immediately for pregnancy testing if onset of menses is delayed or pregnancy is suspected. If the pregnancy test is positive, the physician and patient must discuss the risks to her, the pregnancy, and the fetus [see Dosage and Administration (2.1), Contraindications (4.1), Warnings and Precautions (5.3)].

Contraception

Drug interaction studies show that bosentan reduces serum levels of the estrogen and progestin in oral contraceptives. Based on these findings, hormonal contraceptives (including oral, injectable, transdermal, and implantable contraceptives) may be less effective for preventing pregnancy in patients using TRACLEER and should not be used as a patient's only contraceptive method [see Drug Interactions (7.2)] . Females of reproductive potential using TRACLEER should use effective methods of contraception prior to initiation of treatment, during treatment, and for 1 month after treatment with TRACLEER [see Warnings and Precautions (5.3)]. Patients may choose one highly effective form of contraception (intrauterine devices (IUD) or tubal sterilization) or a combination of methods (hormone method with a barrier method or two barrier methods). If a partner's vasectomy is the chosen method of contraception, a hormone or barrier method must be used along with this method. Counsel patients on pregnancy planning and prevention, including emergency contraception, or designate counseling by another healthcare provider trained in contraceptive counseling.

Infertility

Males

Decreased sperm counts have been observed in patients receiving TRACLEER. Based on these findings and findings in animals, TRACLEER may impair fertility in males of reproductive potential. It is not known whether effects on fertility would be reversible [see Warnings and Precautions (5.6), Adverse Reactions (6.1), Nonclinical Toxicology (13.1)] .

8.4 Pediatric Use

The efficacy of TRACLEER in patients <18 years is supported by data from an uncontrolled trial in which 19 pediatric patients were treated with TRACLEER. In this study, cardiopulmonary hemodynamic improvements were similar to those seen in adults treated with TRACLEER [see Clinical Studies (14.1)] . Safety in pediatric patients is supported by data from 100 pediatric patients treated with TRACLEER for a median of 17 months [see Adverse Reactions (6.1), Clinical Studies (14.1)] .

Juvenile Animal Toxicity Data

In a juvenile rat toxicity study, rats were treated from Day 4 postpartum to adulthood (Day 69 postpartum). Decreased body weights, absolute weights of testes and epididymides, and reduced number of sperm in epididymides were observed after weaning. No effect on testis histology or sperm morphology and function was seen. The NOAEL was 4 times (at Day 4 postpartum) and 2 times (Day 69 postpartum) the human therapeutic exposure, respectively.

No effects on general development, sensory, cognitive function and reproductive performance were detected at the highest dose tested in juvenile rats, 7 times the therapeutic exposure in children with PAH.

8.5 Geriatric Use

Clinical studies of TRACLEER did not include sufficient numbers of subjects aged 65 and older to determine whether they respond differently from younger subjects.

8.6 Hepatic Impairment

Because there is in vitro and in vivo evidence that the main route of excretion of bosentan is biliary, liver impairment could be expected to increase exposure (Cmax and AUC) of bosentan. The pharmacokinetics of TRACLEER have not been evaluated in patients with severe liver impairment (Child-Pugh Class C). In patients with moderate hepatic impairment (Child-Pugh Class B), the systemic exposures to bosentan and its active metabolite increased significantly. TRACLEER should generally be avoided in patients with moderate or severe liver impairment. Pharmacokinetics of bosentan were not altered in patients with mild impairment of hepatic function (Child-Pugh Class A) [see Dosage and Administration (2.6), Warnings and Precautions (5.1), Clinical Pharmacology (12.3)] .

8.7 Renal Impairment

The effect of renal impairment on the pharmacokinetics of bosentan is small and does not require dosing adjustment [see Clinical Pharmacology (12.3)] .

10 OVERDOSAGE

Bosentan has been given as a single dose of up to 2400 mg in normal volunteers, or up to 2000 mg/day for 2 months in patients, without any major clinical consequences. The most common side effect was headache of mild to moderate intensity. In the cyclosporine A interaction study, in which doses of 500 and 1000 mg twice daily of bosentan were given concomitantly with cyclosporine A, trough plasma concentrations of bosentan increased 30-fold, resulting in severe headache, nausea, and vomiting, but no serious adverse events. Mild decreases in blood pressure and increases in heart rate were observed.

In the postmarketing period, there was one reported overdose of 10,000 mg of TRACLEER taken by an adolescent male patient. He had symptoms of nausea, vomiting, hypotension, dizziness, sweating, and blurred vision. He recovered within 24 hours with blood pressure support.

Bosentan is unlikely to be effectively removed by dialysis due to the high molecular weight and extensive plasma protein binding.

11 DESCRIPTION

TRACLEER® is the proprietary name for bosentan, an endothelin receptor antagonist that belongs to a class of highly substituted pyrimidine derivatives, with no chiral centers. It is designated chemically as 4-tert-butyl-N-[6-(2-hydroxy-ethoxy)-5-(2-methoxy-phenoxy)-[2,2´]-bipyrimidin-4-yl]- benzenesulfonamide monohydrate and has the following structural formula:

Bosentan has a molecular weight of 569.64 and a molecular formula of C27H29N5O6S∙H2O. Bosentan is a white to yellowish powder. It is poorly soluble in water (1.0 mg/100 mL) and in aqueous solutions at low pH (0.1 mg/100 mL at pH 1.1 and 4.0; 0.2 mg/100 mL at pH 5.0). Solubility increases at higher pH values (43 mg/100 mL at pH 7.5). In the solid state, bosentan is very stable, is not hygroscopic and is not light sensitive.

TRACLEER is available as 62.5 mg and 125 mg film-coated tablets for oral administration, and contains the following excipients: corn starch, ethylcellulose, glyceryl behenate, hydroxypropylmethylcellulose, iron oxide red, iron oxide yellow, magnesium stearate, povidone, pregelatinized starch, sodium starch glycolate, talc, titanium dioxide, and triacetin. Each TRACLEER 62.5 mg tablet contains 64.54 mg of bosentan monohydrate, equivalent to 62.5 mg of anhydrous bosentan. Each TRACLEER 125 mg tablet contains 129.08 mg of bosentan monohydrate, equivalent to 125 mg of anhydrous bosentan.

TRACLEER is also available as a 32 mg tablet for oral suspension and contains the following excipients: acesulfame potassium, aspartame (E951), calcium hydrogen phosphate anhydrous, cellulose microcrystalline, croscarmellose sodium, magnesium stearate, silica colloidal anhydrous, tartaric acid, and tutti frutti flavor. Each dispersible tablet contains 1.87 mg of phenylalanine. Each dispersible tablet contains 33.045 mg of bosentan monohydrate, equivalent to 32 mg anhydrous bosentan.

12 CLINICAL PHARMACOLOGY

12.1 Mechanism of Action

Bosentan is a specific and competitive antagonist at endothelin receptor types ETA and ETB. Bosentan has a slightly higher affinity for ETA receptors than for ETB receptors. The clinical impact of dual endothelin blockage is unknown.

Endothelin-1 (ET-1) is a neurohormone, the effects of which are mediated by binding to ETA and ETB receptors in the endothelium and vascular smooth muscle. ET-1 concentrations are elevated in plasma and lung tissue of patients with PAH, suggesting a pathogenic role for ET-1 in this disease.

12.3 Pharmacokinetics

General

After oral administration, maximum plasma concentrations of bosentan are attained within 3–5 hours and the terminal elimination half-life is about 5 hours in healthy adult subjects. The exposure to bosentan after intravenous and oral administration is about twice as high in adult patients with PAH as it is in healthy adult subjects.

In a relative bioavailability study in healthy adults, the peak plasma concentration and area under the plasma concentration-time curve for bosentan are on an average 14% and 11%, respectively, lower following administration of the oral dispersible tablet compared to the film-coated tablet.

Absorption

The absolute bioavailability of bosentan in normal volunteers is about 50% and is unaffected by food.

Bosentan is highly bound (>98%) to plasma proteins, mainly albumin. Bosentan does not penetrate into erythrocytes. The volume of distribution is about 18 L.

Elimination

Metabolism

Bosentan has three metabolites, one of which is pharmacologically active and may contribute 10%–20% of the effect of bosentan. Bosentan is an inducer of CYP2C9 and CYP3A and possibly also of CYP2C19. Upon multiple oral dosing, plasma concentrations in healthy adults decrease gradually to 50–65% of those seen after single dose administration, probably the effect of auto-induction of the metabolizing liver enzymes. Steady-state is reached within 3–5 days.

Excretion

Bosentan is eliminated by biliary excretion following metabolism in the liver. Less than 3% of an administered oral dose is recovered in urine. Total clearance after a single intravenous dose is about 4 L/h in patients with PAH.

Specific Populations

Pediatrics

The average plasma exposure to bosentan at steady state (AUCss) in pediatric patients with PAH aged 3 to 15 years treated with 31.25, 62.5 or 125 mg (approximately 2 mg/kg) film-coated tablet twice daily is 37% lower than that observed in adult patients with PAH receiving 125 mg film-coated tablet twice daily. Following administration of 4 mg/kg twice daily doses of dispersible tablet in patients with PAH aged 2 to 11 years, the average systemic exposure to bosentan at steady state is similar to that observed with 2 mg/kg. The average exposure to bosentan in these pediatric patients was approximately half the exposure in adult patients treated with 125 mg film-coated tablets twice daily.

The exposure to bosentan at 2 mg/kg three times daily dosing of dispersible tablet is similar to that of 2 mg/kg twice daily dosing in patients with PAH aged 3 months to 12 years.

Based on these findings, exposure to bosentan reaches a plateau at lower doses in pediatric patients than in adults, and doses higher than 2 mg/kg twice daily do not increase the exposure to bosentan in pediatric patients.

Hepatic Impairment

In vitroand in vivoevidence showing extensive hepatic metabolism of bosentan suggests that liver impairment could significantly increase exposure to bosentan. In a study comparing 8 patients with mild liver impairment (Child-Pugh Class A) to 8 controls, the single- and multiple-dose pharmacokinetics of bosentan were not altered in patients with mild hepatic impairment.

In another small (N=8) pharmacokinetic study, the steady-state AUC of bosentan was on average 4.7 times higher and the active metabolite Ro 48-5033 was 12.4 times higher in 5 patients with moderately impaired liver function (Child-Pugh Class B) and PAH associated with portal hypertension than in 3 patients with normal liver function and PAH of other etiologies.

The pharmacokinetics of TRACLEER have not been evaluated in patients with severe liver impairment (Child-Pugh Class C) [see Dosage and Administration (2.2), Warnings and Precautions (5.1), Use in Specific Populations (8.6)] .

Renal Impairment

In patients with severe renal impairment (creatinine clearance 15–30 mL/min), plasma concentrations of bosentan were essentially unchanged and plasma concentrations of the three metabolites were increased about 2-fold compared to subjects with normal renal function. These differences do not appear to be clinically important.

Drug Interactions

Ketoconazole

Co-administration of bosentan 125 mg twice daily and ketoconazole, a potent CYP3A inhibitor, increased the plasma concentrations of bosentan by approximately 100% in normal volunteers. No dose adjustment of TRACLEER is necessary, but increased effects of TRACLEER should be considered.

Warfarin

Co-administration of bosentan 500 mg twice daily for 6 days in normal volunteers decreased the plasma concentrations of both S-warfarin (a CYP2C9 substrate) and R-warfarin (a CYP3A substrate) by 29 and 38%, respectively. Clinical experience with concomitant administration of TRACLEER and warfarin in patients with PAH did not show clinically relevant changes in INR or warfarin dose (baseline vs. end of the clinical studies), and the need to change the warfarin dose during the trials due to changes in INR or due to adverse events was similar among TRACLEER- and placebo-treated patients.

Digoxin, Nimodipine, and Losartan

Bosentan has no significant pharmacokinetic interactions with digoxin and nimodipine, and losartan has no significant effect on plasma levels of bosentan.

Sildenafil

In normal volunteers, co-administration of multiple doses of 125 mg twice daily bosentan and 80 mg three times daily sildenafil resulted in a reduction of sildenafil plasma concentrations by 63% and increased bosentan plasma concentrations by 50%. The changes in plasma concentrations were not considered clinically relevant and dose adjustments are not necessary. This recommendation holds true when sildenafil is used for the treatment of PAH or erectile dysfunction.

Tadalafil

Bosentan (125 mg twice daily) reduced tadalafil (40 mg once per day) systemic exposure (AUC) by 42% and Cmax by 27% following multiple dose co-administration. Tadalafil did not affect the exposure (AUC and Cmax) of bosentan or its metabolites.

Figure 3. CYP Induction-mediated effect of bosentan on other drugs

Figure 4. Effects of other drugs on bosentan

13 NONCLINICAL TOXICOLOGY

13.1 Carcinogenesis, Mutagenesis, Impairment of Fertility

Carcinogenesis and Mutagenesis

Two years of dietary administration of bosentan to mice produced an increased incidence of hepatocellular adenomas and carcinomas in males at doses as low as 450 mg/kg/day (about 8 times the maximum recommended human dose [MRHD] of 125 mg twice daily, on a mg/m^2 basis). In the same study, doses greater than 2000 mg/kg/day (about 32 times the MRHD) were associated with an increased incidence of colon adenomas in both males and females. In rats, dietary administration of bosentan for two years was associated with an increased incidence of brain astrocytomas in males at doses as low as 500 mg/kg/day (about 16 times the MRHD). In a comprehensive battery of in vitro tests (the microbial mutagenesis assay, the unscheduled DNA synthesis assay, the V-79 mammalian cell mutagenesis assay, and human lymphocyte assay) and an in vivo mouse micronucleus assay, there was no evidence for any mutagenic or clastogenic activity of bosentan.

Impairment of Fertility/Testicular Function

The development of testicular tubular atrophy and impaired fertility has been linked with the chronic administration of certain endothelin receptor antagonists in rodents.

Treatment with bosentan at oral doses of up to 1500 mg/kg/day (50 times the MRHD on a mg/m^2 basis) or intravenous doses up to 40 mg/kg/day had no effects on sperm count, sperm motility, mating performance or fertility in male and female rats. An increased incidence of testicular tubular atrophy was observed in rats given bosentan orally at doses as low as 125 mg/kg/ day (about 4 times the MRHD and the lowest doses tested) for two years but not at doses as high as 1500 mg/kg/day (about 50 times the MRHD) for 6 months. Effects on sperm count and motility were evaluated only in the much shorter duration fertility studies in which males had been exposed to the drug for 4–6 weeks. An increased incidence of tubular atrophy was not observed in mice treated for 2 years at doses up to 4500 mg/kg/day (about 75 times the MRHD) or in dogs treated up to 12 months at doses up to 500 mg/kg/day (about 50 times the MRHD).

14 CLINICAL STUDIES

14.1 Pulmonary Arterial Hypertension

WHO Functional Class III-IV

Two randomized, double-blind, multi-center, placebo-controlled trials were conducted in 32 and 213 patients. The larger study (BREATHE-1) compared 2 doses (125 mg twice daily and 250 mg twice daily) of TRACLEER with placebo. The smaller study (Study 351) compared 125 mg twice daily with placebo. Patients had severe (WHO functional Class III–IV) PAH: idiopathic or heritable PAH (72%) or PAH associated with scleroderma or other connective tissue diseases (21%), or to autoimmune diseases (7%). There were no patients with PAH associated with other conditions such as HIV disease or recurrent pulmonary emboli.

In both studies, TRACLEER or placebo was added to patients' current therapy, which could have included a combination of digoxin, anticoagulants, diuretics, and vasodilators (e.g., calcium channel blockers, ACE inhibitors), but not epoprostenol. TRACLEER was given at a dose of 62.5 mg twice daily for 4 weeks and then at 125 mg twice daily or 250 mg twice daily for either 12 (BREATHE-1) or 8 (Study 351) additional weeks. The primary study endpoint was 6-minute walk distance. In addition, symptoms and functional status were assessed. Hemodynamic measurements were made at 12 weeks in Study 351.

The mean age was about 49 years. About 80% of patients were female, and about 80% were Caucasian. Patients had been diagnosed with pulmonary hypertension for a mean of 2.4 years.

Submaximal Exercise Ability

Results of the 6-minute walk distance at 3 months (Study 351) or 4 months (BREATHE-1) are shown in Table 4.

Table 4: Effects of TRACLEER on 6-Minute Walk Distance
 | BREATHE-1 |  |  | Study 351
 | TRACLEER 125 mg twice daily (n=74) | TRACLEER 250 mg twice daily (n=70) | Placebo (n=69) | TRACLEER 125 mg twice daily (n=21) | Placebo (n=11)
Baseline | 326 ± 73 | 333 ± 75 | 344 ± 76 | 360 ± 86 | 355 ± 82
End point | 353 ± 115 | 379 ± 101 | 336 ± 129 | 431 ± 66 | 350 ± 147
Change from baseline | 27 ± 75 | 46 ± 62 | -8 ± 96 | 70 ± 56 | -6 ± 121
Placebo – subtracted | 35 [p=0.01; by Wilcoxon;] | 54 [p=0.0001; by Wilcoxon;] |  | 76 [p=0.02; by Student's t-test.]
Distance in meters: mean ± standard deviation. Changes are to week 16 for BREATHE-1 and to week 12 for Study 351.

In both trials, treatment with TRACLEER resulted in a significant increase in exercise ability. The improvement in walk distance was apparent after 1 month of treatment (with 62.5 mg twice daily) and fully developed by about 2 months of treatment (Figure 5). It was maintained for up to 7 months of double-blind treatment. Walking distance was somewhat greater with 250 mg twice daily, but the potential for increased hepatotoxicity causes this dose not to be recommended [see Dosage and Administration (2.2)] . There were no apparent differences in treatment effects on walk distance among subgroups analyzed by demographic factors, baseline disease severity, or disease etiology, but the studies had little power to detect such differences.

Figure 5. Mean Change in 6-min Walk Distance (BREATHE-1)

Change from baseline in 6-minute walking distance from start of therapy to week 16 in the placebo and combined TRACLEER (125 mg twice daily and 250 mg twice daily) groups. Values are expressed as mean ± standard error of the mean.

Hemodynamic Changes

Invasive hemodynamic parameters were assessed in Study 351. Treatment with TRACLEER led to a significant increase in cardiac index (CI) associated with a significant reduction in pulmonary artery pressure (PAP), pulmonary vascular resistance (PVR), and mean right atrial pressure (RAP) (Table 5).

The relationship between hemodynamic effects and improvements in 6-minute walk distance is unknown.

Table 5: Change from Baseline to Week 12: Hemodynamic Parameters
 | TRACLEER 125 mg twice daily |  | Placebo
CI (L/min/m^2) | n=20 |  | n=10
Baseline | 2.35±0.73 |  | 2.48±1.03
Absolute Change | 0.50±0.46 |  | -0.52±0.48
Treatment Effect |  | 1.02 [p≤0.001;]
Mean PAP (mmHg) | n=20 |  | n=10
Baseline | 53.7±13.4 |  | 55.7±10.5
Absolute Change | -1.6±5.1 |  | 5.1±8.8
Treatment Effect |  | -6.7 [p<0.02]
PVR (dyn∙sec∙cm^-5) | n=19 |  | n=10
Baseline | 896±425 |  | 942±430
Absolute Change | -223±245 |  | 191±235
Treatment Effect |  | -415
Mean RAP (mmHg) | n=19 |  | n=10
Baseline | 9.7±5.6 |  | 9.9±4.1
Absolute Change | -1.3±4.1 |  | 4.9±4.6
Treatment Effect |  | -6.2
Values shown are means ± SD

Symptoms and Functional Status

Symptoms of PAH were assessed by Borg dyspnea score, WHO functional class, and rate of "clinical worsening." Clinical worsening was assessed as the sum of death, hospitalizations for PAH, discontinuation of therapy because of PAH, and need for epoprostenol. There was a significant reduction in dyspnea during walk tests (Borg dyspnea score), and significant improvement in WHO functional class in TRACLEER-treated patients. There was a significant reduction in the rate of clinical worsening (Table 6 and Figure 6). Figure 6 shows the log-rank test reflecting clinical worsening over 28 weeks.

Table 6: Incidence of Clinical Worsening, Intent To Treat Population
 | BREATHE-1 |  | Study 351
 | TRACLEER 125/250 mg twice daily (n=144) | Placebo (n=69) | TRACLEER 125 mg twice daily (n=21) | Placebo (n=11)
Patients with clinical worsening [n (%)] | 9 (6%) [p=0.0015 vs. placebo by log-rank test. There was no relevant difference between the 125 mg and 250 mg twice daily groups.] | 14 (20%) | 0 (0%) [p=0.033 vs. placebo by Fisher's exact test.] | 3 (27%)
Death | 1 (1%) | 2 (3%) | 0 (0%) | 0 (0%)
Hospitalization for PAH | 6 (4%) | 9 (13%) | 0 (0%) | 3 (27%)
Discontinuation due to worsening of PAH | 5 (3%) | 6 (9%) | 0 (0%) | 3 (27%)
Receipt of epoprostenol [Receipt of epoprostenol was always a consequence of clinical worsening.] | 4 (3%) | 3 (4%) | 0 (0%) | 3 (27%)
Note: Patients may have had more than one reason for clinical worsening.

Figure 6. Time to Clinical Worsening (BREATHE-1)

Time from randomization to clinical worsening with Kaplan-Meier estimate of the proportions of failures in BREATHE-1. All patients (n=144 in the TRACLEER group and n=69 in the placebo group) participated in the first 16 weeks of the study. A subset of this population (n=35 in the TRACLEER group and 13 in the placebo group) continued double-blind therapy for up to 28 weeks.

WHO Functional Class II

In a randomized, double-blind, multicenter, placebo-controlled trial, 185 mildly symptomatic PAH patients with WHO Functional Class II (mean baseline 6-minute walk distance of 443 meters) received TRACLEER 62.5 mg twice daily for 4 weeks followed by 125 mg twice daily (n=93), or placebo (n=92) for 6 months. Enrolled patients were treatment-naïve (n=156) or on a stable dose of sildenafil (n=29). The coprimary endpoints were change from baseline to month 6 in PVR and 6-minute walk distance. Time to clinical worsening (assessed as the sum of death, hospitalization due to PAH complications, or symptomatic progression of PAH), Borg dyspnea index, change in WHO functional class and hemodynamics were assessed as secondary endpoints.

Compared with placebo, TRACLEER treatment was associated with a reduced incidence of worsening of at least one functional class (3% TRACLEER vs. 13% placebo, p=0.03), and improvement in hemodynamic variables (PVR, mPAP, TPR, cardiac index, and SVO2; p <0.05). The +19 m mean (+14 m median) increase in 6-minute walk distance with TRACLEER vs. placebo was not significant (p=0.08). There was a significant delay in time to clinical worsening (first seen primarily as symptomatic progression of PAH) with TRACLEER compared with placebo (hazard ratio 0.2, p=0.01). Findings were consistent in strata with or without treatment with sildenafil at baseline.

Long-term Treatment of PAH

Long-term follow-up of patients with Class III and IV PAH who were treated with TRACLEER in open-label extensions of trials (N=235) showed that 93% and 84% of patients were still alive at 1 and 2 years, respectively, after the start of treatment.

These uncontrolled observations do not allow comparison with a group not given TRACLEER and cannot be used to determine the long-term effect of TRACLEER on mortality.

Pediatric Studies

The efficacy of bosentan was evaluated in an open-label, uncontrolled study in 19 pediatric patients with PAH aged 3 to 15 years. Patients had primary pulmonary hypertension (n=10) or PAH related to congenital heart diseases (9 patients) and were WHO functional class II (n=15, 79%) or class III (n=4; 21%) at baseline. Patients were dosed with bosentan at approximately 2 mg/kg twice daily (body weight adjusted dose, corresponding to the recommended adult dose) [see Dosage and Administration (2.1)] for 12 weeks. Half of the patients in each group were already being treated with intravenous epoprostenol and the dose of epoprostenol remained constant for the duration of the study.

Hemodynamics were measured in 17 patients (Table 7). The mean decrease in PVR was 389 dyn∙sec∙cm^-5, which was similar to the effect seen in adults. Hemodynamic improvements from baseline were similar with or without co-administration of epoprostenol.

Table 7: Change from Baseline to Week 12: Hemodynamic Parameters
 | TRACLEER 2 mg/kg twice daily
CI (L/min/m^2) | n=17
Baseline | 4.0±1.5
Absolute Change | 0.5±1.4
Mean PAP (mmHg) | n=18
Baseline | 60±18
Absolute Change | -8±9
PVR (dyn∙sec∙cm^-5) | n=17
Baseline | 1195±755
Absolute Change | -389±616
Mean RAP (mmHg) | n=18
Baseline | 6.1±2.7
Absolute Change | -0.5±2.3
Values shown are means ± SD

Pulmonary Arterial Hypertension in Adults related to Congenital Heart Disease with Left-to-Right Shunts

A small study (N=54) and its open-label extension (N=37) of up to 40 weeks in adult patients with Eisenmenger physiology demonstrated effects of TRACLEER on exercise and safety that were similar to those seen in other trials in patients with PAH (WHO Group 1).

14.2 Lack of Benefit in Congestive Heart Failure

TRACLEER is not effective in the treatment of congestive heart failure with left ventricular dysfunction. In a pair of studies, 1613 subjects with NYHA Class III-IV heart failure, left ventricular ejection fraction <35%, on diuretics, ACE inhibitor, and other therapies, were randomized to placebo or TRACLEER (62.5 mg twice daily titrated as tolerated to 125 mg twice daily) and followed for up to 70 weeks. Use of TRACLEER was associated with no benefit on patient global assessment (the primary end point) or mortality. However, hospitalizations for heart failure were more common during the first 4 to 8 weeks after TRACLEER was initiated. In a placebo-controlled trial of patients with severe chronic heart failure, there was an increased incidence of hospitalization for CHF associated with weight gain and increased leg edema during the first 4–8 weeks of treatment with TRACLEER. Patients required intervention with a diuretic, fluid management, or hospitalization for decompensating heart failure.

16 HOW SUPPLIED/STORAGE AND HANDLING

62.5 mgfilm-coated, round, biconvex, orange-white tablets, debossed with identification marking "62,5", packaged in a white high-density polyethylene bottle and a white polypropylene child-resistant cap or in foil blister-strips for hospital unit-dosing.

NDC 66215-101-06: Bottle containing 60 tablets.

NDC 66215-101-03: Carton of 30 tablets in 10 blister strips of 3 tablets.

125 mgfilm-coated, oval, biconvex, orange-white tablets, debossed with identification marking "125", packaged in a white high-density polyethylene bottle and a white polypropylene child-resistant cap or in foil blister-strips for hospital unit-dosing.

NDC 66215-102-06: Bottle containing 60 tablets.

NDC 66215-102-03: Carton of 30 tablets in 10 blister strips of 3 tablets.

32 mgtablets for oral suspension, pale yellow to off-white, round, bisected on one side and debossed with identification marking "32" on the other side, packaged in child-resistant Aluminum/Aluminum peel-push blisters.

NDC 66215-232-56: Carton of 56 tablets for oral suspension in 4 blister-strips of 14 tablets.

NDC 66215-232-14: Blister strip of 14 tablets for oral suspension.

STORAGE AND HANDLING

Store at 20 ºC to 25 ºC (68 ºF to 77 ºF). Excursions are permitted between 15 °C and 30 °C (59 °F and 86 °F). [See USP Controlled Room Temperature]. These storage temperatures apply to both film-coated and dispersible tablets. Divided dispersible tablets should be stored under the same conditions and used within 7 days. Tablet pieces may be returned to the opened blister and stored there out of reach of children for up to 7 days.

Keep out of reach of children.

17 PATIENT COUNSELING INFORMATION

Advise the patient to read the FDA-approved patient labeling (Medication Guide)

Restricted Access

Advise the patient that TRACLEER is only available through a restricted access program called the Bosentan REMS and that TRACLEER is available only from certified pharmacies enrolled in the Bosentan REMS.

As a component of the Bosentan REMS, prescribers must review the contents of the TRACLEER Medication Guide with the patient before initiating TRACLEER and patients must sign the Patient Enrollment Form to confirm that they understand the risks of TRACLEER.

Instruct patients that the risks associated with TRACLEER include hepatotoxicity. Discuss with the patient the requirement to measure serum aminotransferases monthly [see Dosage and Administration (2.1, 2.4), Warnings and Precautions (5.1, 5.2)].

Embryo-Fetal Toxicity

Counsel female patients of reproductive potential about the need to use effective contraception prior to treatment, during treatment with TRACLEER and for one month after treatment discontinuation. Females of reproductive potential should have a negative pregnancy test prior to treatment [see Dosage and Administration (2.1), Warnings and Precautions (5.3), Drug Interactions (7.2), Use in Specific Populations (8.1, 8.3)].

Patients should be instructed to immediately contact their physician if they suspect they may be pregnant. Patients should seek additional contraceptive advice from a gynecologist or similar expert as needed.

Educate and counsel females of reproductive potential on the use of emergency contraception in the event of unprotected sex or contraceptive failure.

Advise pre-pubertal females to report any changes in their reproductive status immediately to her prescriber.

Lactation

Advise women not to breastfeed during treatment with TRACLEER [see Use in Specific Populations (8.2)].

Infertility

Advise males of reproductive potential that TRACLEER may impair fertility [see Warnings and Precautions (5.6), Adverse Reactions (6.1), Use in Specific Populations (8.3) and Nonclinical Toxicology (13.1)].

Phenylketonurics

TRACLEER dispersible tablets contain phenylalanine, a component of aspartame. Each dispersible tablet contains 1.87 mg of phenylalanine.

Other Risks Associated with TRACLEER

Instruct patients that the risks associated with TRACLEER also include the following:

- Decreases in hemoglobin and hematocrit – advise patients of the importance of hemoglobin testing,
- Decreases in sperm count,
- Fluid retention.

Manufactured for:
Actelion Pharmaceuticals US, Inc.
Titusville, NJ 08560, USA

For patent information: www.janssenpatents.com

© Johnson & Johnson and its affiliates 2001 – 2019

Medication Guide
TRACLEER® (TRA-KLEER)
(BOSENTAN)
TABLETS

Read the Medication Guide that comes with TRACLEER before you start taking it and each time you get a refill. There may be new information. This Medication Guide does not take the place of talking with your healthcare provider about your medical condition or your treatment.

What is the most important information I should know about TRACLEER?
TRACLEER can cause serious side effects including:
Liver damage.

- Liver damage may not cause symptoms at first. Only a blood test can show if you have early liver damage. You must have your blood tested to check your liver function before you start TRACLEER and each month after that. Your healthcare provider will order these tests. Regular blood tests are important because they will help your healthcare provider adjust or stop your treatment before there is permanent damage.
- Tell your healthcare provider if you have had liver problems, including liver problems while taking other medicines. Call your healthcare provider right away if you have any of these symptoms of liver problems while taking TRACLEER:
  - nausea
  - vomiting
  - fever
  - unusual tiredness
  - stomach area (abdominal) pain
  - yellowing of the skin or the whites of your eyes (jaundice)

Because of the risk for liver damage, TRACLEER is only available through a restricted program called the Bosentan REMS. Before you begin taking TRACLEER, you must read and agree to all of the requirements of the Bosentan REMS. Serious birth defects.

- TRACLEER can cause serious birth defects if taken during pregnancy. You should not be pregnant when you start taking TRACLEER or during TRACLEER treatment. Serious birth defects from TRACLEER may happen early in pregnancy. Females who are able to get pregnant should have a negative pregnancy test before starting treatment with TRACLEER.
  - Talk to your healthcare provider about your menstrual cycle. Your healthcare provider will decide when to do a pregnancy test and will order a pregnancy test for you depending on your menstrual cycle.
    - Females who are ableto get pregnant are females who:
      - have entered puberty, even if they have not started their menstrual period, and
      - have a uterus, and
      - have not gone through menopause. Menopause means that you have not had a menstrual period for at least 12 months for natural reasons, or that you have had your ovaries removed.
    - Females who are not ableto get pregnant are females who:
      - have not yet entered puberty, or
      - do not have a uterus, or
      - have gone through menopause. Menopause means that you have not had a menstrual period for at least 12 months for natural reasons, or that you have had your ovaries removed or
      - are infertile for other medical reasons and this infertility is permanent and cannot be reversed.
    - Females who are able to get pregnant should use effective birth control prior to starting treatment with TRACLEER, during treatment with TRACLEER, and for one month after stopping TRACLEER because the medicine may still be in the body.
      - Talk with your healthcare provider or gynecologist (a doctor who specializes in female reproduction) to find out about options for effective birth control that you may use to prevent pregnancy during treatment with TRACLEER.
      - If you decide that you want to change the form of birth control that you use, talk with your healthcare provider or gynecologist to be sure that you choose another acceptable form of birth control.
      - Do not have unprotected sex. Talk to your healthcare provider or pharmacist right away if you have unprotected sex or if you think your birth control has failed. Your healthcare provider may talk with you about using emergency birth control.
      - Tell your healthcare provider right away if you miss a menstrual period or think you may be pregnant.
    If you are the parent or caregiver of a female child who started taking TRACLEER before reaching puberty, you should check your child regularly to see if she is developing signs of puberty. Tell your healthcare provider right away if you notice that she is developing breast buds or any pubic hair. Your healthcare provider should decide if your child has reached puberty. Your child may reach puberty before having her first menstrual period.

TRACLEER 32 mg dispersible tablets contain Aspartame. Phenylketonurics: Contains Phenylalanine 1.87 mg per 32 mg dispersible tablet.
See " What are the possible side effects of TRACLEER?" for more information about side effects.

What is TRACLEER?
TRACLEER is a prescription medicine used to treat people with certain types of pulmonary arterial hypertension (PAH), which is high blood pressure in the vessels of the lungs.
TRACLEER can improve your ability to exercise and can slow the worsening of your physical condition and symptoms. TRACLEER lowers high blood pressure in your lungs and lets your heart pump blood more efficiently.
TRACLEER is only:
Prescribed by healthcare providers who are enrolled in the Bosentan REMS.
Available to people who understand the risks and requirements and agree to enroll in the Bosentan REMS.

Who should not take TRACLEER?
Do not take TRACLEER if you:

- are pregnant, plan to become pregnant, or become pregnant during TRACLEER treatment. TRACLEER can cause serious birth defects.All females should read the birth defectssection of " What is the most important information I should know about TRACLEER?"
- take any of these medicines:
  - cyclosporine A used to treat psoriasis and rheumatoid arthritis, and to prevent rejection of heart, liver, and kidney transplants
  - glyburide used to treat diabetes
- are allergic to bosentan or any of the ingredients in TRACLEER. See the end of this Medication Guide for a complete list of the ingredients in TRACLEER. If you have a rash, hives or your lips swell after taking TRACLEER, it may be a sign of allergy. You should stop taking your TRACLEER and talk to your healthcare provider.

What should I tell my healthcare provider before taking TRACLEER?
TRACLEER may not be right for you. Tell your healthcare provider about all your medical conditions, including if you:

- have liver problems.
- are pregnant or plan to become pregnant. See “What is the most important information I should know about TRACLEER?”
- are breast-feeding or plan to breast feed. TRACLEER passes into your breast milk. It is not known if TRACLEER in breast milk can harm your baby. You and your healthcare provider should decide if you will take TRACLEER or breastfeed.

Tell your healthcare provider about all the medicines you take, including prescription and over-the-counter medicines, vitamins, and herbal supplements. TRACLEER and other medicines may affect how each other works and cause side effects. Especially tell your healthcare provider if you take:

- hormone-based birth control, such as pills, shots, patches, and implants. These birth control methods may not work as well when taken with TRACLEER.
- simvastatin or other "-statin" medicines used to lower cholesterol
- rifampin used for tuberculosis
- ketoconazole, fluconazole, itraconazole, or voriconazole used for fungal infections
- warfarin sodium used to prevent blood clots
- ritonavir used to treat HIV

There may be more than one brand name medicine. Ask your healthcare provider if you are not sure if your medicine is one that is listed above.
Know the medicines you take. Keep a list of them and show it to your healthcare provider or pharmacist when you get a new medicine.

How should I take TRACLEER?
Your healthcare provider will give you detailed information about the Bosentan REMS.

- TRACLEER is only available through certified pharmacies. You will only receive a 30-day supply of TRACLEER at one time.
- Take TRACLEER exactly as prescribed.
- Your healthcare provider will tell you how much TRACLEER to take and when to take it.
- In most cases, you will take 1 tablet in the morning and 1 in the evening.
- You can take TRACLEER orally with or without food.
- If you take more than the prescribed dose of TRACLEER, call your healthcare provider right away.
- If you miss a dose of TRACLEER, take your tablet as soon as you remember. Do not take 2 doses at the same time. If it is almost time for your next dose, skip the missed dose. Just take the next dose at your regular time.
- Do not stop taking TRACLEER unless your healthcare provider tells you to. Suddenly stopping your treatment may cause your symptoms to get worse. If you need to stop taking TRACLEER, speak with your healthcare provider about the right way to stop.
- If necessary, the 32 mg dispersible tablet can be divided into halves by breaking along a line cut into the surface. Hold the tablet between the thumb and index finger on either side of the line, with the line facing upwards, and break the tablet along the line (see figure below).
- Each 32 mg dispersible tablet, or tablet part, can be dispersed in a minimal amount of water to make a liquid medicine immediately before administration. When the tablet has fully dispersed, the liquid should be administered to the patient.

What are the possible side effects of TRACLEER?
TRACLEER can cause serious side effects, including:

- See " What is the most important information I should know about TRACLEER?"
- Fluid retention and swelling of your ankles and legs. TRACLEER can cause your body to hold too much water, and you may get swelling of your ankles and legs. Tell your healthcare provider if you have swelling of your ankles and legs that happens either with or without weight gain, or if you have more trouble with your breathing than normal. Your healthcare provider will look for the cause of this.
- Lower Sperm Count. Some men who take TRACLEER may have lower sperm counts. This may affect your ability to father a child. Tell your healthcare provider if fertility is a concern for you.
- Low red blood cell levels (anemia). Your healthcare provider will do blood tests to check your red blood cells during treatment with TRACLEER.

The most common side effects of TRACLEER include:

- respiratory tract infection
- headache
- fainting
- flushing
- low blood pressure
- inflamed nose passages (sinusitis)
- joint pain
- irregular heart beats

Tell your doctor if you have any side effect that bothers you or that does not go away. These are not all the possible side effects of TRACLEER. For more information, ask your doctor or pharmacist.
Call your doctor for medical advice about side effects. You may report side effects to FDA at 1-800-FDA-1088.

How should I store TRACLEER?

- Store TRACLEER at room temperature between 68 °F to 77 °F (20 °C to 25 °C).
- Dispersible tablets that have been broken to adjust the dose of medicine can be stored at room temperature, between 68 °F to 77 °F (20 °C to 25 °C), and should be used within 7 days of having been broken. Tablet pieces may be returned to the opened blister and stored there out of reach of children for up to 7 days.

Keep TRACLEER and all medicines out of the reach of children.

General information about TRACLEER
Medicines are sometimes prescribed for purposes other than those listed in a Medication Guide. Do not use TRACLEER for a condition for which it was not prescribed. Do not give TRACLEER to other people, even if they have the same symptoms that you have. It may harm them.
This Medication Guide summarizes the most important information about TRACLEER. If you would like more information, talk with your healthcare provider. You can ask your pharmacist or healthcare provider for information about TRACLEER that is written for health professionals. For more information call 1-800-526-7736, or go to www.TRACLEER.com.

What are the ingredients in TRACLEER?
Active ingredient: bosentan
Inactive ingredients in 62.5 mg and 125 mg film-coated tablets: corn starch, ethylcellulose, glyceryl behenate, hydroxypropylmethylcellulose, iron oxide red, iron oxide yellow, magnesium stearate, povidone, pregelatinized starch, sodium starch glycolate, talc, titanium dioxide, and triacetin.
Inactive ingredients in 32 mg dispersible tablets: acesulfame potassium, aspartame (E951), calcium hydrogen, cellulose microcrystalline, croscarmellose sodium, magnesium stearate, phosphate anhydrous, silica colloidal anhydrous, tartaric acid, and tutti frutti flavor.
Manufactured for:
Actelion Pharmaceuticals US, Inc.
Titusville, NJ 08560, USA
For patent information: www.janssenpatents.com
© Johnson & Johnson and its affiliates 2001 – 2019

This Medication Guide has been approved by the U.S. Food and Drug Administration.

Revised: 11/2025

PRINCIPAL DISPLAY PANEL - 62.5 mg Tablet Bottle Carton

NDC 66215-101-06

Tracleer®
(bosentan) tablets
62.5 mg

Attention: Dispense with
enclosed Medication Guide.

Rx only

60 film-coated tablets

janssen

PRINCIPAL DISPLAY PANEL - 125 mg Tablet Bottle Carton

NDC 66215-102-06

Tracleer®
(bosentan) tablets
125 mg

Attention: Dispense with
enclosed Medication Guide.

Rx only

60 film-coated tablets

janssen

PRINCIPAL DISPLAY PANEL - 32 mg Tablet Blister Pack Carton - 232

NDC 66215-232-56

Tracleer®
(bosentan) Tablets for Oral Suspension

32 mg

Phenylketonurics:
Contains Phenylalanine
1.87 mg per tablet for oral suspension

Rx only

Contains: 56 tablets for oral suspension per carton.
Each carton contains 4 blister-strips of 14 tablets each.

Attention: Dispense with
enclosed Medication Guide.

This package is child-resistant.

Store this medicine out of
the reach of children.

janssen